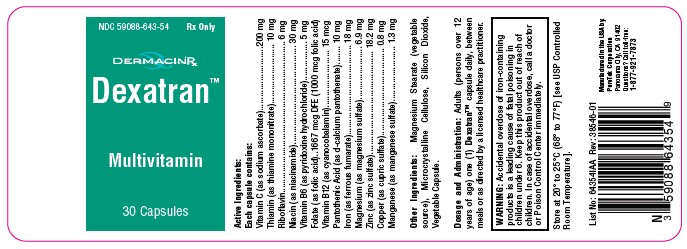 DRUG LABEL: Dexatran
NDC: 59088-643 | Form: CAPSULE
Manufacturer: PureTek Corporation
Category: prescription | Type: HUMAN PRESCRIPTION DRUG LABEL
Date: 20240913

ACTIVE INGREDIENTS: MAGNESIUM SULFATE HEPTAHYDRATE 6.9 mg/1 1; RIBOFLAVIN 6 mg/1 1; NIACINAMIDE 30 mg/1 1; PYRIDOXINE HYDROCHLORIDE 5 mg/1 1; FOLIC ACID 1 mg/1 1; CYANOCOBALAMIN 15 ug/1 1; CALCIUM PANTOTHENATE 10 mg/1 1; SODIUM ASCORBATE 200 mg/1 1; THIAMINE MONONITRATE 10 mg/1 1; ZINC SULFATE 18.2 mg/1 1; MANGANESE SULFATE 1.3 mg/1 1; FERROUS FUMARATE 18 mg/1 1; CUPRIC SULFATE 0.8 mg/1 1
INACTIVE INGREDIENTS: SILICON DIOXIDE; MICROCRYSTALLINE CELLULOSE; GELLAN GUM (LOW ACYL); HYPROMELLOSES; WATER; MAGNESIUM STEARATE

Dexatran Multivitamin

DESCRIPTION:

Active ingredients:
Each capsule contains:
Vitamin C (as sodium ascorbate).................................200 mg
Thiamin (as thiamine mononitrate)............................... 10 mg
Riboflavin....................................................................... 6 mg
Niacin (as niacinamide)................................................ 30 mg
Vitamin B6 (as pyridoxine hydrochloride)....................... 5 mg
Folate (as folic acid)...... 1667 mcg DFE (1000 mcg folic acid)
Vitamin B12 (as cyanocobalamin).............................. 15 mcg
Pantothenic Acid (as d-calcium pantothenate)............. 10 mg
Iron (as ferrous fumarate)............................................ 18 mg
Magnesium (as magnesium sulfate)............................ 6.9 mg
Zinc (as zinc sulfate).................................................. 18.2 mg
Copper (as cupric sulfate)........................................... 0.8 mg
Manganese (as manganese sulfate)............................ 1.3 mg

Other Ingredients:
Magnesium Stearate (vegetable source), Microcrystalline Cellulose, Silicon Dioxide, Vegetable Capsule.

Indications and Usage:

Dexatran™ is indicated to provide dietary management for men and women. Folic acid is effective in the treatment of megaloblastic anemias due to a deficiency of folic acid (as may be seen in tropical or nontropical sprue) and in anemias of nutritional origin, pregnancy, infancy, or childhood.

Contraindications:

This product is contraindicated in patients with known hypersensitivity to any of its ingredients; also, all iron compounds are contraindicated in patients with hemosiderosis, hemochromatosis, or hemolytic anemias. Pernicious anemia is a contraindication, as folic acid may obscure its signs and symptoms.

Warnings:

Accidental overdose of iron-containing products is a leading cause of fatal poisoning in children under 6. Keep this product out of reach of children. In case of accidental overdose, call a doctor or Poison Control Center immediately.

Administration of folic acid alone is improper therapy for pernicious anemia and other megaloblastic anemias in which vitamin B12 is deficient.

Precautions:

Folic acid in doses above 0.1 mg daily may obscure pernicious anemia, in that hematologic remission can occur while neurological manifestations remain progressive.

There is a potential danger in administering folic acid to patients with undiagnosed anemia, since folic acid may obscure the diagnosis of pernicious anemia by alleviating the hematologic manifestations of the disease while allowing the neurologic complications to progress. This may result in severe nervous system damage before the correct diagnosis is made. Adequate doses of vitamin B12 may prevent, halt, or improve the neurologic changes caused by pernicious anemia.

The patient’s medical conditions and consumption of other drugs, herbs, and/or supplements should be considered.

For use on the order of a healthcare practitioner.

Call your doctor about side effects. To report side effects, call PureTek Corporation at 1-877-921-7873 or FDA at 1-800-FDA-1088 or www.fda.gov/medwatch.

Drug Interactions:

Dexatran™ is not recommended for and should not be given to patients receiving levodopa because the action of levodopa is antagonized by pyridoxine. There is a possibility of increased bleeding due to pyridoxine interaction with anticoagulants (e.g., Aspirin, Heparin or Clopidogrel).

Adverse Reactions:

Folic Acid: Allergic sensitizations has been reported following both oral and parenteral administration of folic acid.

Ferrous Fumarate: Gastrointestinal disturbances (anorexia, nausea, diarrhea, constipation) occur occasionally, but are usually mild and may subside with continuation of therapy. Although the absorption of iron is best when taken between meals, giving Dexatran™ after meals may control occasional gastrointestinal disturbances. Dexatran™ is best absorbed when taken at bedtime.

Adverse reactions have been reported with specific vitamins and minerals but generally at levels substantially higher than those contained herein. However, allergic and idiosyncratic reactions are possible at lower levels. Iron, even at the usual recommended levels, has been associated with gastrointestinal intolerance in some patients.

OVERDOSE:

Iron: Signs and Symptoms: Iron is toxic. Acute overdosage of iron may cause nausea and vomiting and, in severe cases, cardiovascular collapse and death. Other symptoms include pallor and cyanosis, melena, shock, drowsiness and coma. The estimated overdose of orally ingested iron is 300 mg/kg body weight. When overdoses are ingested by children, severe reactions, including fatalities, have resulted. Dexatran™ should be stored beyond the reach of children to prevent against accidental iron poisoning. Keep this and all other drugs out of reach of children.

Treatment:

For specific therapy, exchange transfusion and chelating agents shouldbe used. For general management, perform gastric lavage with sodium bicarbonate solution or milk.

Administer intravenous fluids and electrolytes and use oxygen.

Dosage and Administration:

Adults (persons over 12 years of age) one (1) Dexatran™ capsule daily, between meals or as directed by a physician. Do not administer to children under the age of 12.

How Supplied:

Dexatran™ are transparent capsules in bottles containing 30 capsules – NDC 59088-643-54. Dispense in a tight, light-resistant container as defined in the USP/NF with a child resistant closure.

Do not use if bottle seal is broken. KEEP THIS AND ALL MEDICATIONS OUT OF THE REACH OF CHILDREN.
Store at controlled room temperature 20o to 25oC (68o to 77oF). [See USP].
Protect from light and moisture and avoid excessive heat.

Dexatran™

Manufactured in the USA by:
PureTek Corporation
Panorama City, CA 91402
Questions? Call toll-free:
1-877-921-7873